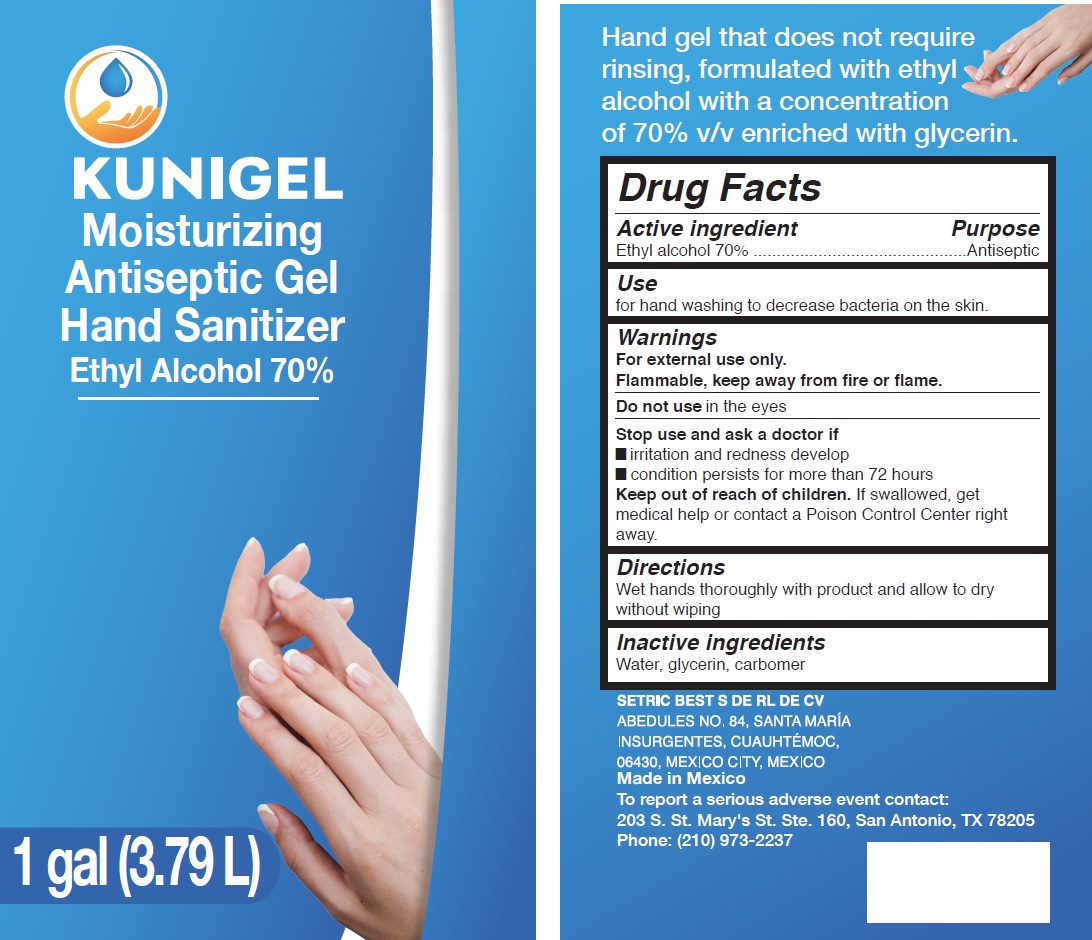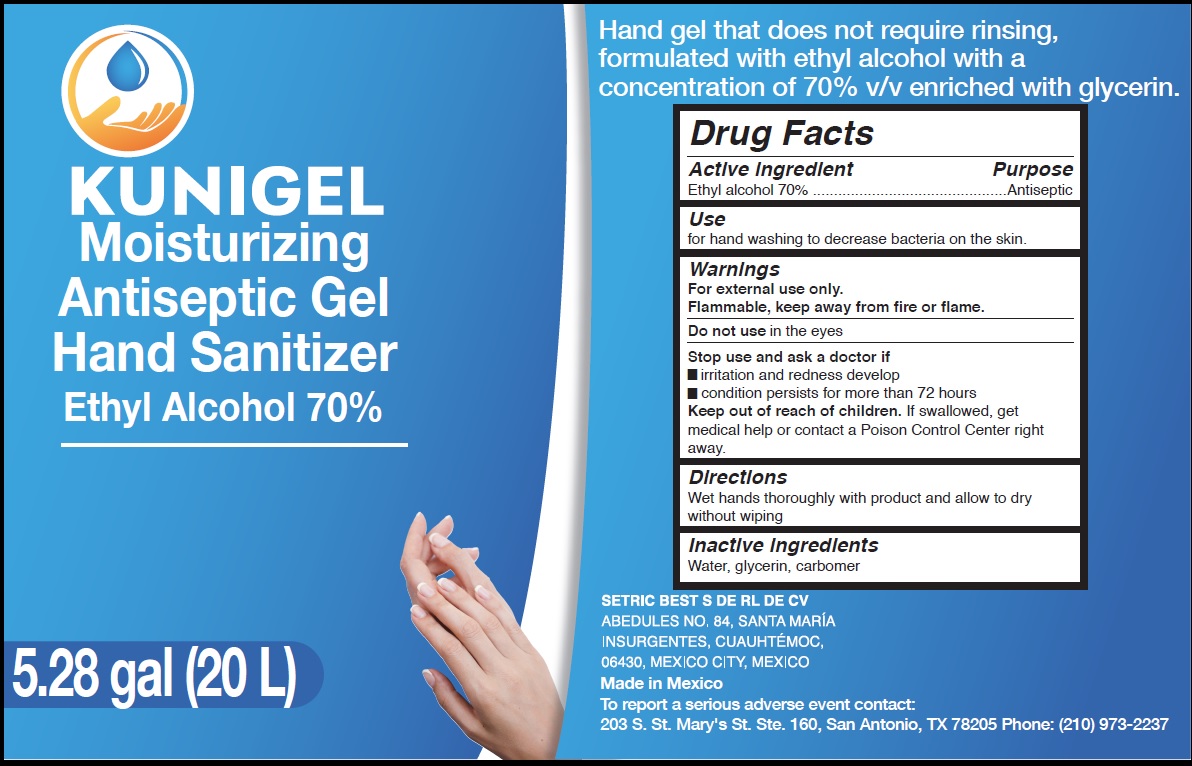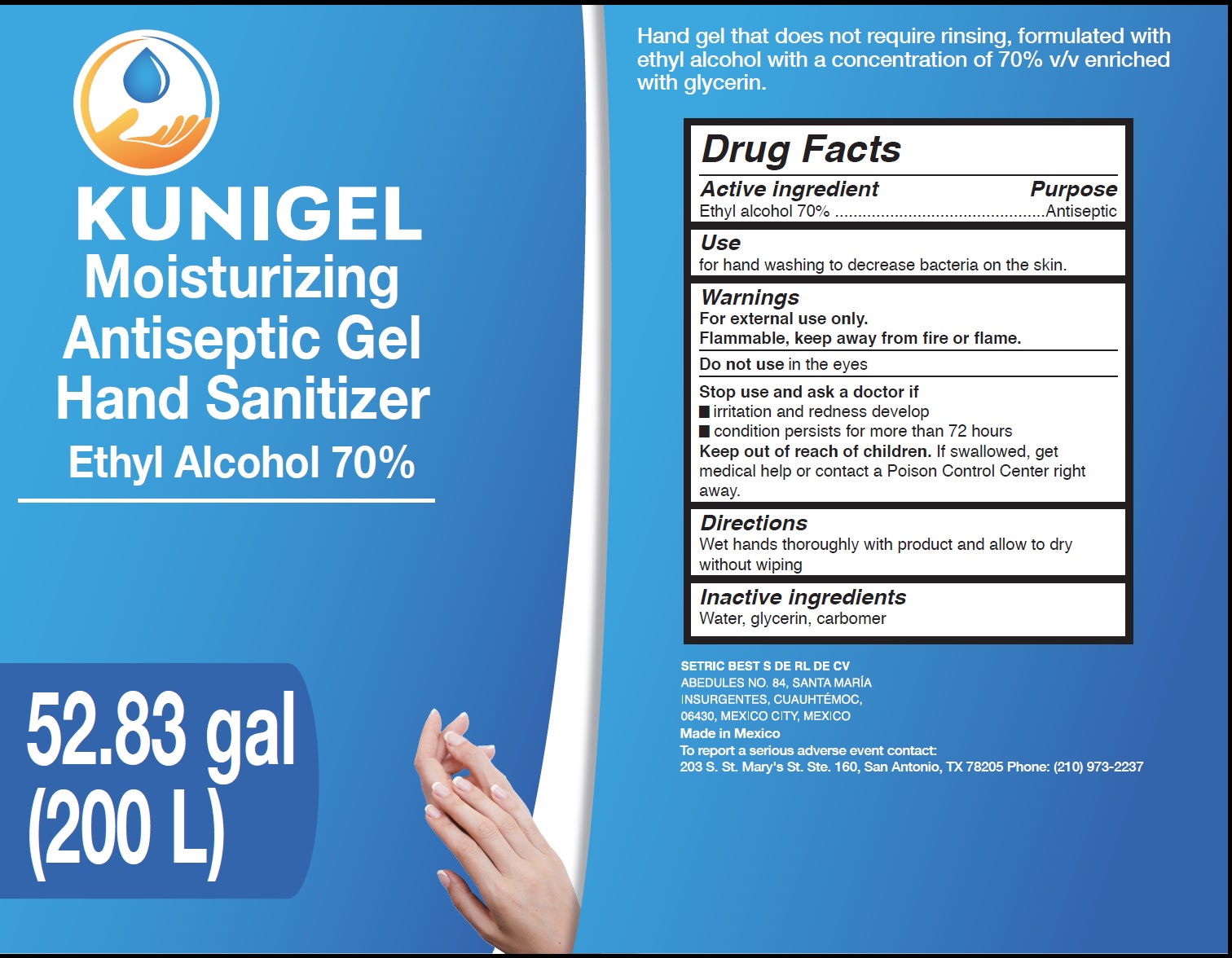 DRUG LABEL: Kunigel Moisturizing Antiseptic Hand Sanitizer
NDC: 81941-000 | Form: GEL
Manufacturer: Setric Best, S. de R.L. de C.V.
Category: otc | Type: HUMAN OTC DRUG LABEL
Date: 20220331

ACTIVE INGREDIENTS: ALCOHOL 70 mL/100 mL
INACTIVE INGREDIENTS: WATER; GLYCERIN; CARBOMER HOMOPOLYMER, UNSPECIFIED TYPE

Kunigel Moisturizing Antiseptic Hand Sanitizer

Active ingredient

Ethyl alcohol 70%

Purpose

Antiseptic

Use

for hand washing to decrease bacteria on the skin.

Warnings

For external use only.
Flammable, keep away from fire or flame.

Do not use

in the eyes

Stop use and ask a doctor if

- irritation and redness develop
- condition persists for more than 72 hours

Keep out of reach of children.

If swallowed, get medical help or contact a Poison Control Center right away.

Directions

Wet hands thoroughly with product and allow to dry without wiping

Inactive ingredients

Water, glycerin, carbomer